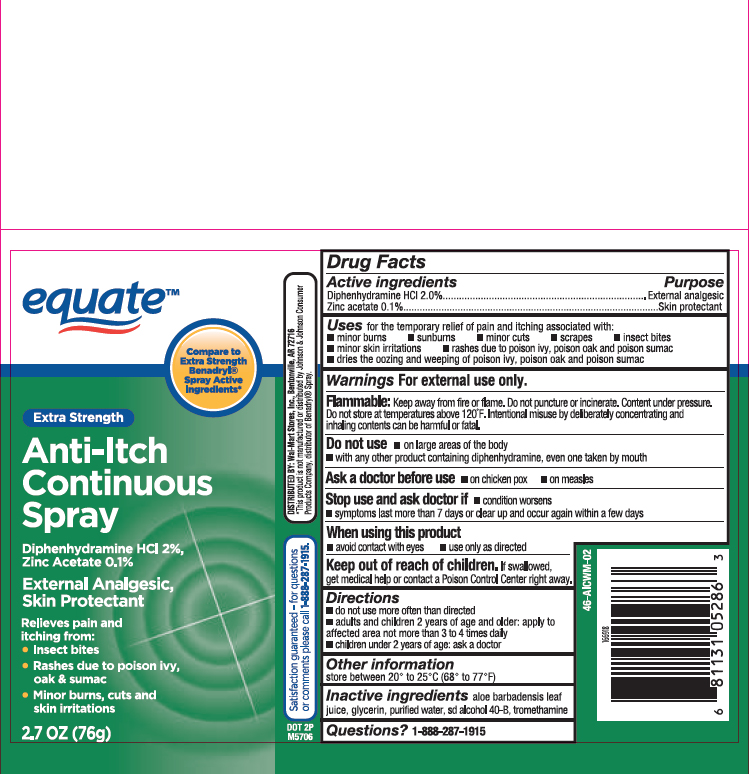 DRUG LABEL: Diphenhydramine HCl and Zinc Acetate
NDC: 49035-015 | Form: AEROSOL, SPRAY
Manufacturer: Wal-Mart Stores, Inc.
Category: otc | Type: HUMAN OTC DRUG LABEL
Date: 20250627

ACTIVE INGREDIENTS: DIPHENHYDRAMINE HYDROCHLORIDE 1.5 g/88 mL; ZINC ACETATE 0.075 g/88 mL
INACTIVE INGREDIENTS: GLYCERIN; WATER; ALCOHOL; TROMETHAMINE; ALOE VERA LEAF

Equate Extra Strength Anti-Itch Continuous Spray

Active ingredients

Diphenhydramine HCl 2%,
Zinc Acetate 0.1%

Purpose

External analgesic

Skin protectant

Uses

for the temporary relief of pain and itching associated with:

- minor burns
- sunburns
- minor cuts
- scrapes
- insect bites
- minor skin irritations
- rashes due to poison ivy, poison oak and poison sumac
- dries the oozing and weeping of poison ivy, poison oak and poison sumac

Warnings

For external use only.

Flammable:

Keep away from fire or flame. Do not puncture or incinerate. Contents under pressure. Do not store at temperatures above 120°F

Do not use

- on large areas of the body
- with any other product containing diphenhydramine, even one taken by mouth

Stop use and ask doctor if

- conditions worsens
- symptoms last more than 7 days or clear up and occur again within a few days

When using this product

- avoid contact with eyes
- use only as directed

Keep out of reach of children.

If swallowed, get medical help or contact a Poison Control Center right away.

Directions

- adults and children 2 years of age and older: apply to affected area not more than 3 to 4 times daily
- children under 2 years of age: ask a doctor

Other information

store between 20° to 25°C (68° to 77°F)

Inactive ingredients

aloe barbadensis leaf juice, glycerin, purified water, sd alcohol 40-B, tromethamine

Questions?

1-888-287-1915

Principal Display Panel

Equate

Extra Strength
Anti-Itch Continuous Spray

Diphenhydramine HCl 2%,
Zinc Acetate 0.1%

External Analgesic,
Skin Protectant

Relieves pain and
itching from:

- Insect bites
- Rashes due to poison ivy, oak & sumac
- Minor burns, cuts and skin irritations

2.7 OZ (76 g)